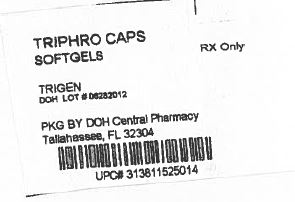 DRUG LABEL: TriphroCaps
NDC: 53808-0987 | Form: CAPSULE
Manufacturer: State of Florida DOH Central Pharmacy
Category: other | Type: DIETARY SUPPLEMENT
Date: 20140424

ACTIVE INGREDIENTS: FOLIC ACID 1 mg/1 1; ASCORBIC ACID 100 mg/1 1; NIACINAMIDE 20 mg/1 1; THIAMINE MONONITRATE 1.5 mg/1 1; RIBOFLAVIN 1.7 mg/1 1; PYRIDOXINE HYDROCHLORIDE 10 mg/1 1; CYANOCOBALAMIN 6 ug/1 1; CALCIUM PANTOTHENATE 5 mg/1 1; BIOTIN 150 ug/1 1
INACTIVE INGREDIENTS: SOYBEAN OIL; GELATIN; GLYCERIN; WATER; YELLOW WAX; TITANIUM DIOXIDE; FD&C RED NO. 40; ETHYL VANILLIN; FD&C YELLOW NO. 5; FD&C YELLOW NO. 6; FERRIC OXIDE RED

TriphroCaps
Softgels

HEALTH CLAIM

Rx Only

DESCRIPTION

TriphroCaps are an orally administered prescription vitamin for the dietary management of patients with nutritional deficiencies or are in need of nutritional supplementation. TriphroCaps are red, oval softgel capsules, imprinted "T9."

Supplement Facts
Servings per Bottle: 100
Serving Size: 1 Softgel Capsule Each Softgel Capsule contains | %DV Adults & Children 4 Years or More
Folate | 1 mg | 250%
Vitamin C (ascorbic acid) | 100 mg | 167%
Niacin (niacinamide) | 20 mg | 100%
Thiamine (thiamine mononitrate) | 1.5 mg | 100%
Riboflavin | 1.7 mg | 100%
Vitamin B6 (pyridoxine HCl) | 10 mg | 500%
Vitamin B12 (cyanocobalamin) | 6 mcg | 100%
Pantothenic Acid (calcium pantothenate) | 5 mg | 50%
Biotin | 150 mcg | 50%

Inactive Ingredients: Soybean Oil, Gelatin, Glycerin, Purified Water, Yellow Bees Wax, Lecithin, Titanium Dioxide, FD&C Red #40, Ethyl Vanillin, FD&C Yellow #5, FD&C Yellow #6, Iron Oxide.

INDICATIONS AND USAGE

TriphroCaps are indicated for the supplemental requirements of patients with nutritional deficiencies or are in need of nutritional supplementation.

TriphroCaps are an orally administered prescription vitamin for the dietary management of patients with nutritional deficiencies or are in need of nutritional supplementation.

CONTRAINDICATIONS

TriphroCaps is contraindicated in patients with a known hypersensitivity to any of the ingredients.

WARNINGS

Folic acid alone is improper therapy in the treatment of pernicious anemia and other megaloblastic anemias where Vitamin B12 is deficient. Folic acid in doses above 0.1 mg daily may obscure pernicious anemia in that hematologic remission can occur while neurological manifestations remain progressive.

THIS PRODUCT CONTAINS SOY.

PRECAUTIONS

Pediatric Use

Safety and effectiveness in pediatric patients have not been established.

Geriatric Use

Clinical studies on this product have not been performed in sufficient numbers of subjects aged 65 and over to determine whether elderly subjects respond differently from younger subjects. In general, dose selection for elderly patients should be cautious, usually starting at the low end of the dosing range, reflecting the greater frequency of decreased hepatic, renal, or cardiac function of concomitant disease or other drug therapy.

ADVERSE REACTIONS

Allergic sensitization has been reported following both oral and parenteral administration of folic acid.

DOSAGE AND ADMINISTRATION

Take one TriphroCaps softgel daily or as prescribed by a physician. On dialysis days, take one TriphroCaps softgel after dialysis.

HOW SUPPLIED

TriphroCaps are supplied in bottles of 100 softgel capsules.

They are supplied by State of Florida DOH Central Pharmacy as follows:

NDC | Quantity/Form | Color | Source Prod. Code
53808-0987-1 | 30 Capsules in a Blister Pack | RED | 13811-525

STORAGE

Store at 20°-25°C (68°-77°F), excursions permitted to 15°-30°C (59°-86°F) [See USP controlled room temperature].

HEALTH CLAIM

Call your doctor about side effects. You may report side effects by calling 888 9 TRIGEN (888-987-4436).

KEEP OUT OF REACH OF CHILDREN

HEALTH CLAIM

Rx Only

All prescriptions using this product shall be pursuant to state statutes as applicable. This is not an Orange Book product. There are no implied or explicit claims on therapeutic equivalence.

Manufactured for:
TRIGEN Laboratories, Inc., Sayreville, NJ 08872
www.trigenlab.com

This Product was Repackaged By:

State of Florida DOH Central Pharmacy
104-2 Hamilton Park Drive
Tallahassee, FL 32304
United States

PACKAGE LABEL

Label Image for 53808-0987